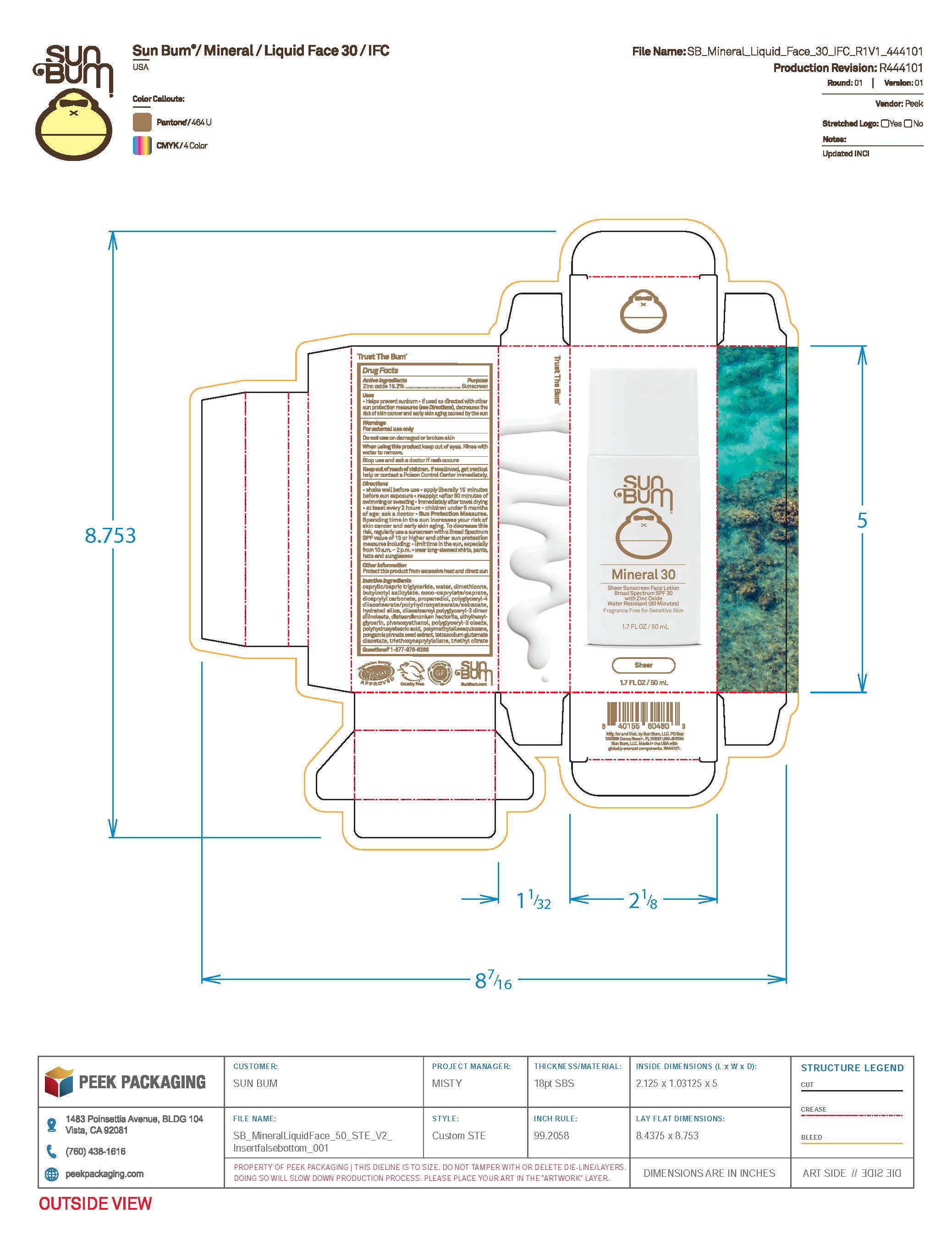 DRUG LABEL: Sun Bum Mineral 30 Sheer Sunscreen Face
NDC: 69039-748 | Form: LOTION
Manufacturer: Sun Bum, LLC
Category: otc | Type: HUMAN OTC DRUG LABEL
Date: 20250815

ACTIVE INGREDIENTS: ZINC OXIDE 192 mg/1 mL
INACTIVE INGREDIENTS: POLYGLYCERYL-4 DIISOSTEARATE/POLYHYDROXYSTEARATE/SEBACATE; COCO-CAPRYLATE/CAPRATE; DIISOSTEAROYL POLYGLYCERYL-3 DIMER DILINOLEATE; TRIETHOXYCAPRYLYLSILANE; WATER; PROPANEDIOL; TRIETHYL CITRATE; ETHYLHEXYLGLYCERIN; CAPRYLIC/CAPRIC TRIGLYCERIDE; DIMETHICONE; BUTYLOCTYL SALICYLATE; HYDRATED SILICA; PHENOXYETHANOL; POLYGLYCERYL-3 OLEATE; TETRASODIUM GLUTAMATE DIACETATE; POLYMETHYLSILSESQUIOXANE (4.5 MICRONS); DICAPRYLYL CARBONATE; DISTEARDIMONIUM HECTORITE; POLYHYDROXYSTEARIC ACID (2300 MW); PONGAMIA PINNATA SEED

Sun Bum Mineral 30 Sheer Sunscreen Face

Active ingredients

Zinc Oxide 19.20%

Purpose

Sunscreen

Uses

• helps prevent sunburn • if used as directed with other sun protection measures, (see Directions) decreases the risk of skin cancer and early skin aging caused by the sun

Warnings

For external use only

Do not use on damaged or broken skin

When using this product keep out of eyes. Rinse with water to remove.

Stop use and ask a doctor if rash occurs

Keep out of reach of children. If swallowed, get medical help or contact a Poison Control Center immediately.

Warnings

Keep Out Of Reach Of Children

Directions

• shake well before use

• apply liberally 15 minutes before sun exposure

• reapply: • after 80 minutes of swimming or sweating • immediately after towel drying • at least every 2 hours

• children under 6 months of age: ask a doctor

• Sun Protection Measures. Spending time in the sun increases your risk of skin cancer and early skin aging. To decrease this risk, regularly use a sunscreen with a Broad Spectrum SPF value of 15 or higher and other sun protection measures including:

• limit time in the sun, especially from 10 a.m.- 2 p.m.

• wear long-sleeved shirts, pants, hats and sunglasses

Directions

• shake well before use

• apply liberally 15 minutes before sun exposure

Other Information

protect this product from excessive heat and direct sun

Inactive Ingredients

caprylic/capric triglyceride, water, dimethicone, butyloctyl salicylate, coco-caprylate/caprate, dicaprylyl carbonate, propanediol, polyglyceryl-4 diisostearate/polyhydroxystearate/sebacate, hydrated silica, diisostearoyl polyglyceryl-3 dimer dilinoleate, disteardimonium hectorite, ethylhexylglycerin, phenoxyethanol, polyglyceryl-3 oleate, polyhydroxystearic acid, polymethylsilsesquioxane, pongamia pinnata seed extract, tetrasodium glutamate diacetate, triethoxycaprylylsilane, triethyl citrate

Questions?

1-877-978-6286